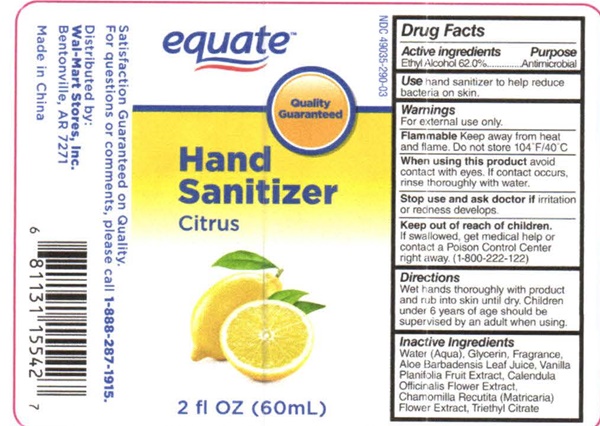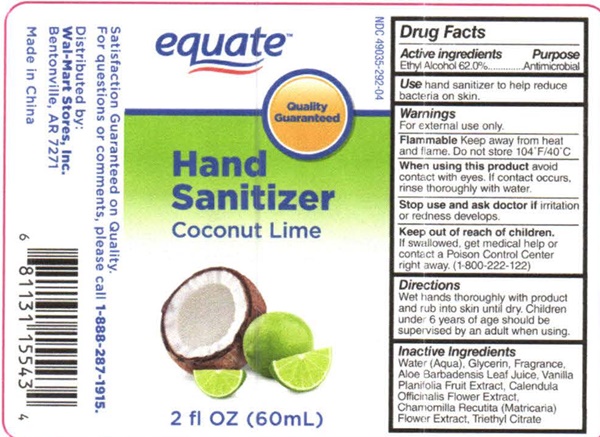 DRUG LABEL: Hand Citrus
NDC: 49035-290 | Form: LIQUID
Manufacturer: Walmart Stores Inc
Category: otc | Type: HUMAN OTC DRUG LABEL
Date: 20161218

ACTIVE INGREDIENTS: ALCOHOL 35.15 g/60 mL
INACTIVE INGREDIENTS: WATER; GLYCERIN; ALOE VERA LEAF; VANILLA PLANIFOLIA OIL; CALENDULA OFFICINALIS FLOWER; MATRICARIA RECUTITA FLOWERING TOP; TRIETHYL CITRATE

Equate Hand Sanitizer - 290, 292

Drug Facts Active ingredients

Ethyl Alcohol 62.0%

Purpose

Antimicrobial

Use

hand sanitizer to help reduce bacteria on skin.

Keep out of reach of children

If swallowed, get medical help or contact a Poison Control Center right away. (1-800-222-122)

Warnings

For external use only.

Flammable

Keep away fron heat and flame. Do not store 104°F (40°C)

When using this product

avoid contact with eyes. If contact occurs, rinse thoroughly with water.

Stop use and ask a doctor if

irritation or redness develops.

Directions

Wet hands thoroughly with product and rub into skin until dry. Children under 6 years of age should be supervised by an adult when using.

Inactive Ingredients

Water (Aqua), Glycerin, Fragrance, Aloe Barbadensis Leaf Juice, Vanilla Planifolia fruit Extract, Calendula Officinalis Flower Extract, Chamomilla Recutita (Matricaria) Flower Extract, Triethyl Citrate

equate Hand Sanitizer Citrus, Coconut Lime

NDC 49035-290-03

equate

Quality Guaranteed

Hand Sanitizer

Citrus

2 fl OZ (60 mL)

Satisfaction Guaranteed on Quality.

For questions or comments, please call 1-888-287-1915.

Distributed by:

Wal-Mart Stores, Inc

Bentonville, AR 7271

Made in China

NDC 49035-292-04

equate

Quality Guaranteed

Hand Sanitizer

Coconut Lime

2 fl OZ (60 mL)

Satisfaction Guaranteed on Quality.

For questions or comments, please call 1-888-287-1915.

Distributed by:

Wal-Mart Stores, Inc

Bentonville, AR 7271

Made in China